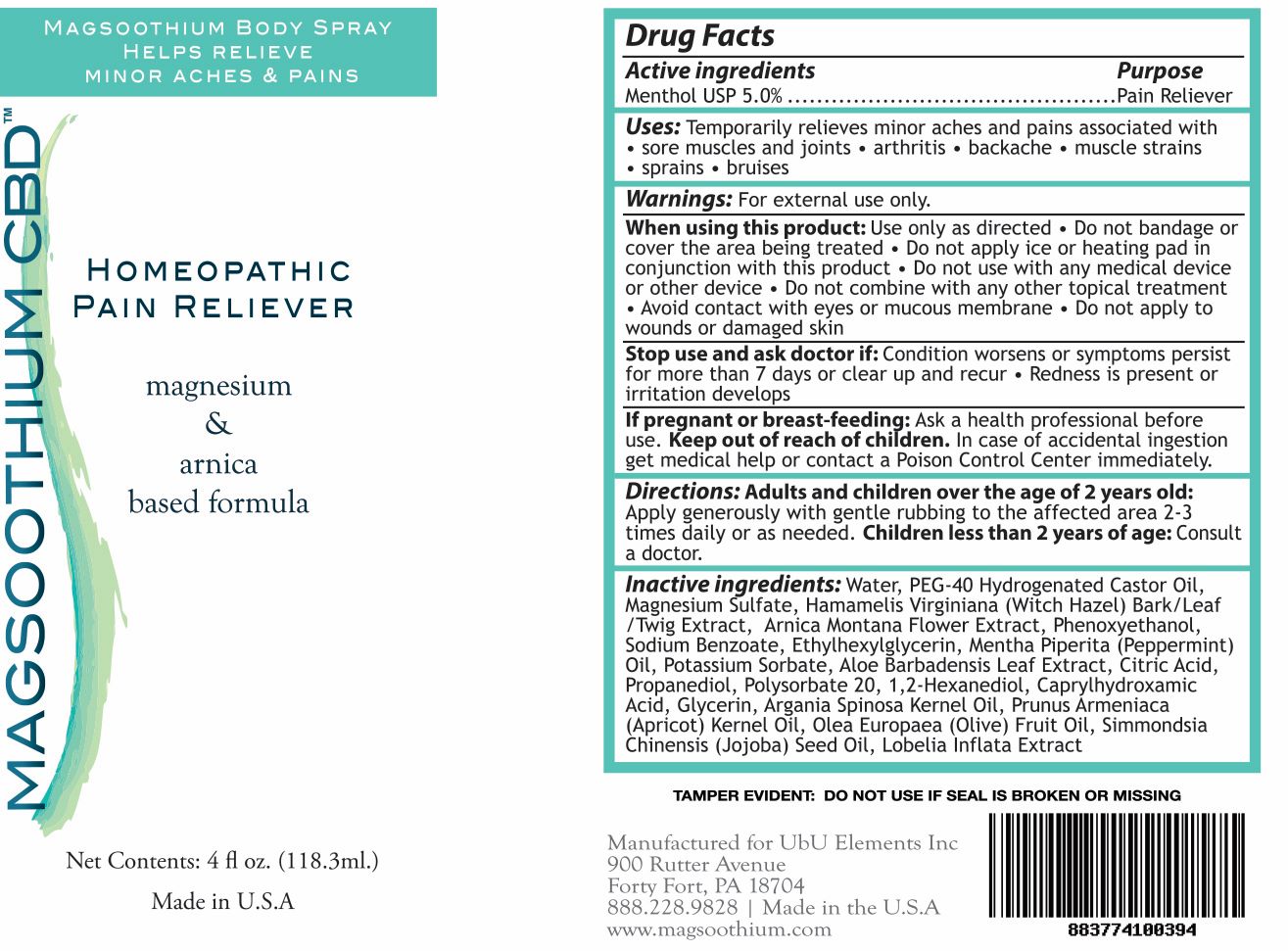 DRUG LABEL: Magsoothium CBD Body
NDC: 83262-004 | Form: SPRAY
Manufacturer: Ubu/Elements, Inc.
Category: otc | Type: HUMAN OTC DRUG LABEL
Date: 20251216

ACTIVE INGREDIENTS: MENTHOL 118 g/100 mL
INACTIVE INGREDIENTS: 1,2-HEXANEDIOL; CAPRYLHYDROXAMIC ACID; LOBELIA INFLATA WHOLE; MAGNESIUM SULFATE, UNSPECIFIED FORM; PROPANEDIOL; CITRIC ACID MONOHYDRATE; POLYSORBATE 20; GLYCERIN; SODIUM BENZOATE; ARNICA MONTANA FLOWER; HAMAMELIS VIRGINIANA TOP; PHENOXYETHANOL; ETHYLHEXYLGLYCERIN; PEPPERMINT OIL; POTASSIUM SORBATE; ALOE VERA LEAF; ARGAN OIL; APRICOT KERNEL OIL; OLIVE OIL; JOJOBA OIL; WATER; POLYOXYL 40 HYDROGENATED CASTOR OIL

Magsoothium CBD Body Spray

Active Ingredients

Menthol USP 5.0%

Purpose

Pain Reliever

PURPOSE

Uses: Temporarily relieves minor aches and pains associated with

- sore muscles and joints
- arthritis
- backache
- muscle strains
- sprains
- bruises

Keep out of reach of children. In case of accidental ingestion get medical help or contact a Poison Control Center immediately.

Stop use and ask a doctor if: Condition worsens or symptoms persist for more than 7 days or clear up and recur

- Redness is present or irritation develops

Warnings: For external use only

When using this product: use only as directed

Do not bandage or cover the area being treated
Do not apply ice or heating pad in conjunction with this product

Do not use with any medical device or other device

Do not combine with any other topical treatment

Avoid contact with eyes or mucous membrane

Do not apply to wounds or damaged skin

If pregnant or breast-feeding: Ask a health professional before use

DOSAGE AND ADMINISTRATION

Directions: Adults and children over the age of 2 years old:

Apply generously with gentle rubbing to the affected area 2-3 times daily or as needed

Children less than 2 years of age: Consult a doctor.

INACTIVE INGREDIENT

Inactive ingredients: Water, PEG-40 Hydrogenated Castor Oil, Magnesium Sulfate Hamamelis Virginiana (Witch Hazel) Bark/Leaf/Twig Extract, Arnica Montana Flower Extract, Phenoxyethanol, Sodium Benzoate, Ethylhexylglycerin, Mentha Piperita (Peppermint) Oil, Potassium Sorbate, Aloe Barbadensis Leaf Extract, Citric Acid, Propanediol, Polysorbate 20, 1,2-Hexanediol, Caprylhydroxamic Acid, Glycerin, Argania Spinosa Kernel Oil, Prunus Armeniaca (Apricot) Kernel Oil, Olea Europaea (Olive) Fruit Oil, Simmondsia Chinensis (Jojoba) Seed Oil, Lobelia inflata Extract

PACKAGE LABEL

Magsoothium Body Spray

Helps Relieve Minor Aches & Pains

Homeopathic Pain Reliever

magnesium & arnica based formula

Net Contents: 4 fl oz. (118.3ml)

Made in U.S.A